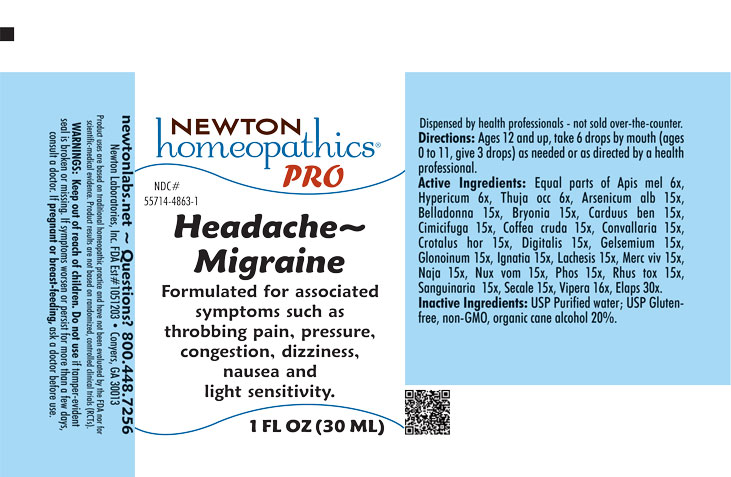 DRUG LABEL: Headache-Migraine
NDC: 55714-4863 | Form: LIQUID
Manufacturer: Newton Laboratories, Inc.
Category: homeopathic | Type: HUMAN OTC DRUG LABEL
Date: 20251202

ACTIVE INGREDIENTS: MICRURUS CORALLINUS VENOM 30 [hp_X]/1 mL; ARSENIC TRIOXIDE 15 [hp_X]/1 mL; ATROPA BELLADONNA 15 [hp_X]/1 mL; BRYONIA ALBA ROOT 15 [hp_X]/1 mL; CENTAUREA BENEDICTA 15 [hp_X]/1 mL; BLACK COHOSH 15 [hp_X]/1 mL; ARABICA COFFEE BEAN 15 [hp_X]/1 mL; CONVALLARIA MAJALIS 15 [hp_X]/1 mL; CROTALUS HORRIDUS HORRIDUS VENOM 15 [hp_X]/1 mL; DIGITALIS 15 [hp_X]/1 mL; LACHESIS MUTA VENOM 15 [hp_X]/1 mL; GELSEMIUM SEMPERVIRENS ROOT 15 [hp_X]/1 mL; NITROGLYCERIN 15 [hp_X]/1 mL; STRYCHNOS IGNATII SEED 15 [hp_X]/1 mL; MERCURY 15 [hp_X]/1 mL; NAJA NAJA VENOM 15 [hp_X]/1 mL; STRYCHNOS NUX-VOMICA SEED 15 [hp_X]/1 mL; PHOSPHORUS 15 [hp_X]/1 mL; TOXICODENDRON PUBESCENS LEAF 15 [hp_X]/1 mL; SANGUINARIA CANADENSIS ROOT 15 [hp_X]/1 mL; CLAVICEPS PURPUREA SCLEROTIUM 15 [hp_X]/1 mL; VIPERA BERUS VENOM 16 [hp_X]/1 mL; APIS MELLIFERA 6 [hp_X]/1 mL; HYPERICUM PERFORATUM 6 [hp_X]/1 mL; THUJA OCCIDENTALIS LEAFY TWIG 6 [hp_X]/1 mL
INACTIVE INGREDIENTS: WATER; ALCOHOL

Headache 4863L

INDICATIONS & USAGE SECTION

Formulated for associated symptoms such as throbbing pain, pressure, congestion, dizziness, nausea and light sensitivity.

DOSAGE & ADMINISTRATION SECTION

Directions: Ages 12 and up, take 6 drops by mouth (ages 0 to 11, give 3 drops) as needed or as directed by a health professional.

OTC - ACTIVE INGREDIENT SECTION

Equal parts of Apis mel 6x, Hypericum 6x, Thuja occ 6x, Arsenicum alb15x, Belladonna 15x, Bryonia 15x, Carduus ben 15x, Cimicifuga 15x, Coffea cruda 15x, Convallaria 15x, Crotalus hor 15x, Digitalis 15x, Gelsemium 15x, Glonoinum 15x, Ignatia 15x, Lachesis 15x, Mercurius viv 15x, Naja 15x, Nux vom 15x, Phos 15x, Rhus tox 15x, Sanguinaria 15x, Secale 15x, Vipera 16x, Elaps 30x.

OTC - PURPOSE SECTION

Formulated for associated symptoms such as throbbing pain, pressure, congestion, dizziness, nausea and light sensitivity.

INACTIVE INGREDIENT SECTION

USP Purified water. USP Gluten-free, non-GMO, organic cane alcohol 20%.

QUESTIONS SECTION

newtonlabs.net – Questions? 800.448.7256

Newton Laboratories, Inc. FDA Est # 1051203 - Conyers, GA 30013

WARNINGS SECTION

WARNINGS: Keep out of reach of children. Do not use if tamper-evident seal is broken or missing. If symptoms worsen or persist for more than a few days, consult a doctor. If pregnant or breast-feeding, ask a doctor before use.

OTC - KEEP OUT OF REACH OF CHILDREN SECTION

Keep out of reach of children

OTC - PREGNANCY OR BREAST FEEDING SECTION

If pregnant or breast-feeding, ask a doctor before use.